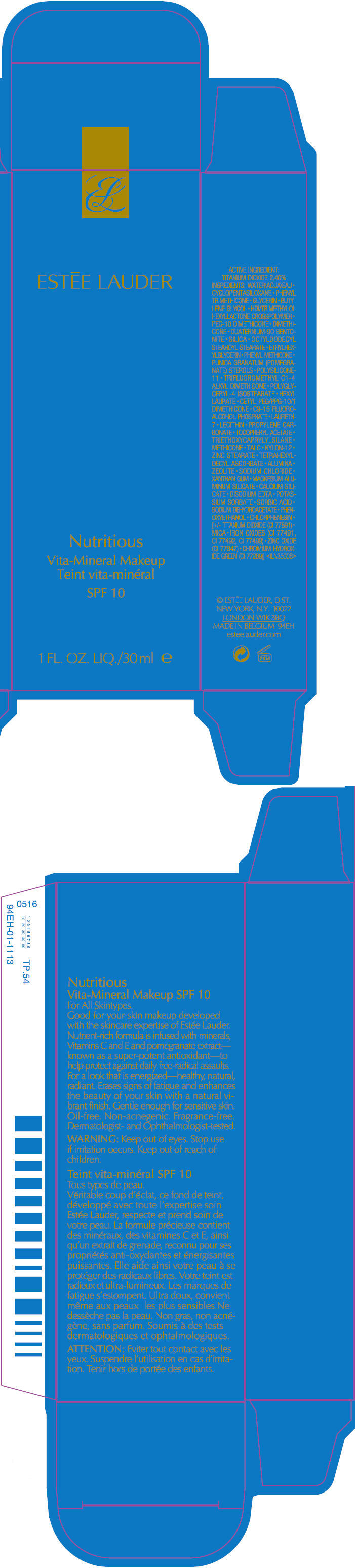 DRUG LABEL: NUTRITIOUS 
NDC: 11559-739 | Form: LIQUID
Manufacturer: Estee Lauder Inc.
Category: otc | Type: HUMAN OTC DRUG LABEL
Date: 20111028

ACTIVE INGREDIENTS: TITANIUM DIOXIDE 2.4 mL/100 mL
INACTIVE INGREDIENTS: WATER; CYCLOMETHICONE 5; PHENYL TRIMETHICONE; GLYCERIN; BUTYLENE GLYCOL; DIMETHICONE; SILICON DIOXIDE; OCTYLDODECYL STEAROYL STEARATE; ETHYLHEXYLGLYCERIN; POLYGLYCERYL-4 ISOSTEARATE; HEXYL LAURATE; LAURETH-7; PROPYLENE CARBONATE; ALPHA-TOCOPHEROL ACETATE; TRIETHOXYCAPRYLYLSILANE; TALC; ZINC STEARATE; TETRAHEXYLDECYL ASCORBATE; ALUMINUM OXIDE; SODIUM CHLORIDE; XANTHAN GUM; MAGNESIUM ALUMINUM SILICATE; CALCIUM SILICATE; EDETATE DISODIUM; POTASSIUM SORBATE; SORBIC ACID; SODIUM DEHYDROACETATE; PHENOXYETHANOL; CHLORPHENESIN; MICA; FERRIC OXIDE RED; FERRIC OXIDE YELLOW; FERROSOFERRIC OXIDE; ZINC OXIDE

Nutritius
Vita-Mineral Makeup
SPF 10

ACTIVE INGREDIENT

TITANIUM DIOXIDE 2.40%

INGREDIENTS

WATER • CYCLOPENTASILOXANE • PHENYL TRIMETHICONE • GLYCERIN • BUTYLENE GLYCOL • HDI/TRIMETHYLOL HEXYLLACTONE CROSSPOLYMER • PEG-10 DIMETHICONE • DIMETHICONE • QUATERNIUM-90 BENTONITE • SILICA • OCTYLDODECYL STEAROYL STEARATE • ETHYLHEXYLGLYCERIN • PHENYL METHICONE • PUNICA GRANATUM (POMEGRANATE) STEROLS • POLYSILICONE-11 • TRIFLUOROMETHYL C1-4 ALKYL DIMETHICONE • POLYGLYCERYL-4 ISOSTEARATE • HEXYL LAURATE • CETYL PEG/PPG-10/1 DIMETHICONE • C9-15 FLUOROALCOHOL PHOSPHATE • LAURETH-7 • LECITHIN • PROPYLENE CARBONATE • TOCOPHERYL ACETATE • TRIETHOXYCAPRYLYLSILANE • METHICONE • TALC • NYLON-12 • ZINC STEARATE • TETRAHEXYLDECYL ASCORBATE • ALUMINA • ZEOLITE • SODIUM CHLORIDE • XANTHAN GUM • MAGNESIUM ALUMINUM SILICATE • CALCIUM SILICATE • DISODIUM EDTA • POTASSIUM SORBATE • SORBIC ACID • SODIUM DEHYDROACETATE • PHENOXYETHANOL • CHLORPHENESIN • [+/- TITANIUM DIOXIDE (CI 77891) • MICA • IRON OXIDES (CI 77491, CI 77492, CI 77499) • ZINC OXIDE (CI 77947) • CHROMIUM HYDROXIDE GREEN (CI 77289)]

WARNING

Keep out of eyes.

Stop use if irritation occurs.

Keep out of reach of children.

© ESTĒE LAUDER, DIST.
NEW YORK, N.Y. 10022

PRINCIPAL DISPLAY PANEL - 30 ml Carton

ESTĒE LAUDER

Nutritious
Vita-Mineral Makeup

SPF 10

1 FL. OZ. LIQ./30 ml e